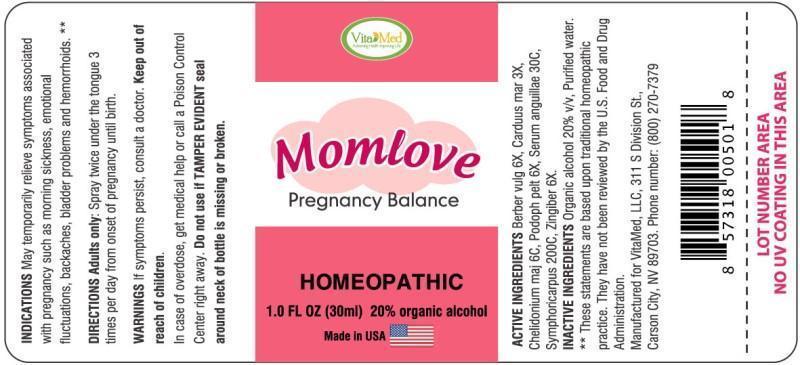 DRUG LABEL: MOMLOVE
NDC: 64249-0004 | Form: SPRAY
Manufacturer: VitaMed, LLC
Category: homeopathic | Type: HUMAN PRESCRIPTION DRUG LABEL
Date: 20140818

ACTIVE INGREDIENTS: BERBERIS VULGARIS ROOT BARK 6 [hp_X]/1 mL; MILK THISTLE 3 [hp_X]/1 mL; CHELIDONIUM MAJUS 6 [hp_C]/1 mL; PODOPHYLLUM 6 [hp_X]/1 mL; ANGUILLA ROSTRATA BLOOD SERUM 30 [hp_C]/1 mL; SYMPHORICARPOS ALBUS FRUIT 200 [hp_C]/1 mL; GINGER 6 [hp_X]/1 mL
INACTIVE INGREDIENTS: WATER; ALCOHOL

DRUG FACTS

ACTIVE INGREDIENTS:

Berberis Vulgaris 6X, Carduus Marianus 3X, Chelidonium Majus 6C, Podophyllum Peltatum 6X, Serum Anguillae 30C, Symphoricarpus Racemosus 200C, Zingiber Officinale 6X

INDICATIONS:

May temporarily relieve symptoms associated with pregnancy such as morning sickness, emotional fluctuations, backaches, bladder problems and hemorrhoids. **

**These statements are based upon traditional homeopathic practice. They have not been reviewed by the U.S. Food and Drug Administration.

WARNINGS:

If symptoms persist, consult a doctor.

Keep out of reach of children. In case of overdose, get medical help or call a Poison Control Center right away.

Do not use if TAMPER EVIDENT seal around neck of bottle is missing or broken.

Keep out of reach of children.In case of overdose, get medical help or call a Poison Control Center right away.

DIRECTIONS:

Adults only: Spray twice under the tongue 3 times per day from onset of pregnancy until birth.

INDICATIONS:

May temporarily relieve symptoms associated with pregnancy such as morning sickness, emotional fluctuations, backaches, bladder problems and hemorrhoids. **

**These statements are based upon traditional homeopathic practice. They have not been reviewed by the U.S. Food and Drug Administration.

INACTIVE INGREDIENTS:

Organic alcohol 20% v/v, Purified water.

QUESTIONS:

Manufactured for VitaMEd, LLC, 311 S Division St.,

Carson City, NV 89703. Phone number: (800) 270-7379

PACKAGE LABEL DISPLAY

Vita Med

Momlove

Pregnancy Balance

HOMEOPATHIC

1.0 Fl OZ (30 ml)